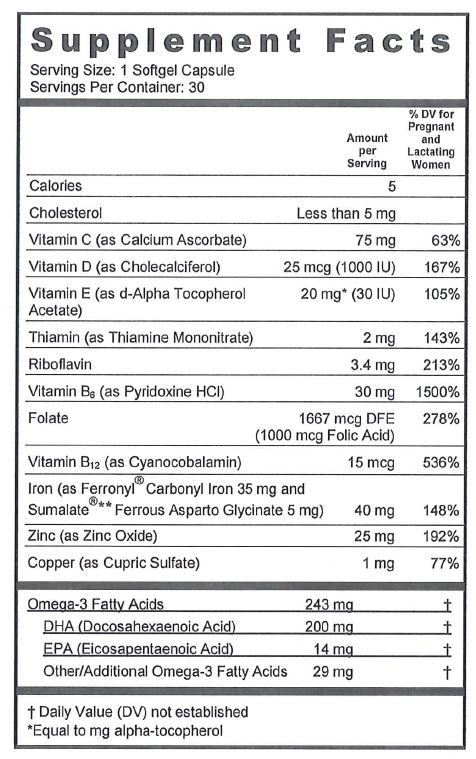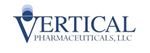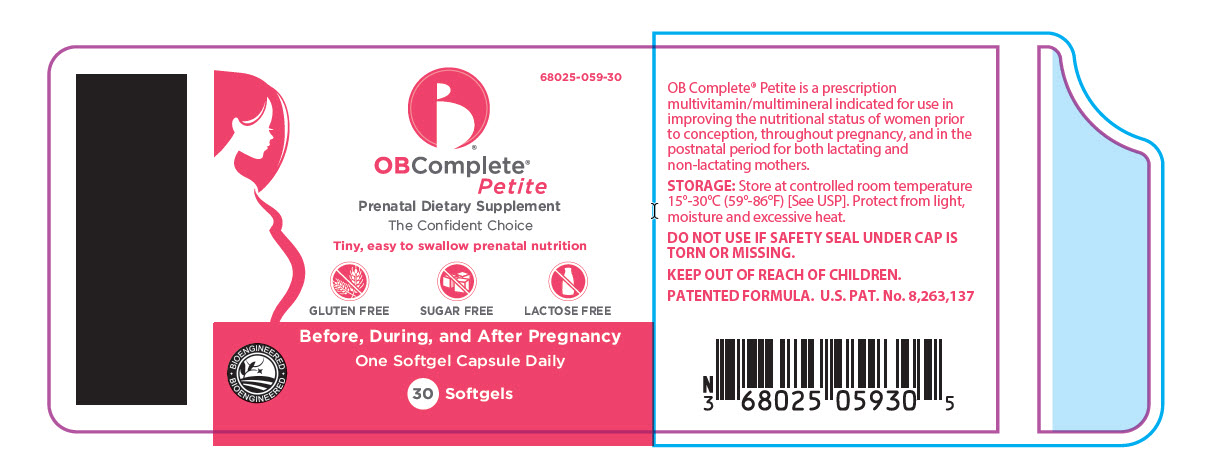 DRUG LABEL: OB Complete Petite
NDC: 68025-059 | Form: CAPSULE, LIQUID FILLED
Manufacturer: Vertical Pharmaceuticals, LLC
Category: other | Type: DIETARY SUPPLEMENT
Date: 20211124

ACTIVE INGREDIENTS: CALCIUM ASCORBATE 75 mg/1 1; CHOLECALCIFEROL 1000 [iU]/1 1; .ALPHA.-TOCOPHEROL ACETATE, D- 30 [iU]/1 1; THIAMINE MONONITRATE 2 mg/1 1; RIBOFLAVIN 3.4 mg/1 1; PYRIDOXINE HYDROCHLORIDE 30 mg/1 1; FOLIC ACID 1 mg/1 1; CYANOCOBALAMIN 15 ug/1 1; IRON 35 mg/1 1; FERROUS ASPARTO GLYCINATE 5 mg/1 1; ZINC OXIDE 25 mg/1 1; CUPRIC SULFATE 1 mg/1 1; DOCONEXENT 200 mg/1 1
INACTIVE INGREDIENTS: SOYBEAN OIL; YELLOW WAX; LECITHIN, SOYBEAN; GELATIN; WATER; TITANIUM DIOXIDE; FD&C RED NO. 40; ETHYL VANILLIN; FD&C BLUE NO. 1

OB Complete® Petite

SUPPLEMENT FACTS

Other Ingredients: Soybean Oil, Yellow Bees Wax, Lecithin, Gelatin, Purified Water, Titanium Dioxide, FD&C Red #40, Ethyl Vanillin, FD&C Blue #1.

CONTAINS: SOY AND FISH OIL (ANCHOVY)

GLUTEN-, LACTOSE-, AND SUGAR-FREE

OB Complete® Petite is a prescription multivitamin/multimineral indicated for use in improving the nutritional status of women prior to conception, throughout pregnancy, and in the postnatal period for both lactating and non-lactating mothers.

CONTRAINDICATIONS

This product is contraindicated in patients with a known hypersensitivity to any of the ingredients.

WARNINGS

WARNING: Accidental overdose of iron-containing products is a leading cause of fatal poisoning in children under 6.

KEEP THIS PRODUCT OUT OF REACH OF CHILDREN. In case of accidental overdose, call a doctor or poison control center immediately.

PRECAUTIONS

Folic acid alone is improper therapy in the treatment of pernicious anemia and other megaloblastic anemias where vitamin B12 is deficient. Folic acid in doses above 0.1 mg daily may obscure pernicious anemia in that hematologic remission can occur while neurologic manifestations remain progressive. Allergic sensitization has been reported following both oral and parenteral administration of folic acid.

The patient’s medical conditions and consumption of other drugs, herbs, and/or supplements should be considered.

DRUG INTERACTIONS

OB Complete®Petite softgel capsules are not recommended for and should not be given to patients receiving levodopa because the action of levodopa is antagonized by pyridoxine. There is a possibility of increased bleeding due to pyridoxine interaction with anticoagulants (e.g., Aspirin, Heparin, Clopidogrel).

ADVERSE REACTIONS

Adverse reactions have been reported with specific vitamins and minerals but generally at levels substantially higher than those contained herein. However, allergic and idiosyncratic reactions are possible at lower levels. Iron, even at the usual recommended levels, has been associated with gastrointestinal intolerance in some patients.

DESCRIPTION

OB Complete® Petite is an oval-shaped plum colored softgel capsule, imprinted "VP 059".

DIRECTIONS FOR USE

One softgel capsule daily or as directed by a physician.

HOW SUPPLIED

OB Complete® Petite is supplied in a 30 count child-resistant bottle.

Product Code: 68025-059-30

STORAGE

Store at controlled room temperature 15°-30°C (59°-86°F) [See USP]. Protect from light, moisture and excessive heat.

KEEP OUT OF REACH OF CHILDREN.

PATENTED FORMULA. U.S. PAT. No. 8,263,137

For use on the order of a healthcare practitioner.

Call your doctor about side effects. To report side effects, call Vertical Pharmaceuticals at 1-770-509-4500 or FDA at 1-800-FDA-1088 or www.fda.gov/medwatch.

Distributed by:

Vertical Pharmaceuticals, LLC

Alpharetta, GA 30005

www.OBComplete.com

PLR-OBCPT-00005-2 Rev. 11/2021

**Ferrous Asparto Glycinate (Sumalate®, a registered trademark of Albion International, Inc.) is covered by the following patents:

U.S. Pat. No. 6,716,814, U.S. Pat. No. 8,007,846 and U.S. Pat. No. 8,425,956.

PRINCIPAL DISPLAY PANEL - 30 Capsule Bottle Label

68025-059-30

OB
COMPLETE®

Petite

Gluten,
Lactose and
Sugar-Free

VERTICAL
PHARMACEUTICALS, LLC

30 SOFTGEL
CAPSULES